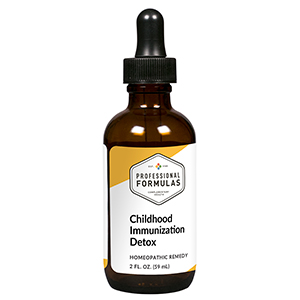 DRUG LABEL: Childhood Immunization Detox
NDC: 63083-6032 | Form: LIQUID
Manufacturer: Professional Complementary Health Formulas
Category: homeopathic | Type: HUMAN OTC DRUG LABEL
Date: 20190815

ACTIVE INGREDIENTS: OYSTER SHELL CALCIUM CARBONATE, CRUDE 3 [hp_X]/59 mL; ECHINACEA ANGUSTIFOLIA WHOLE 3 [hp_X]/59 mL; SILICON DIOXIDE 3 [hp_X]/59 mL; THUJA OCCIDENTALIS LEAF 3 [hp_X]/59 mL; ARSENIC TRIOXIDE 6 [hp_X]/59 mL; SULFUR 6 [hp_X]/59 mL; MELANDRIN 30 [hp_X]/59 mL; L-3972-T 60 [hp_X]/59 mL; HEPATITIS A VIRUS STRAIN HM175 ANTIGEN (FORMALDEHYDE INACTIVATED) 60 [hp_X]/59 mL; MYCOBACTERIUM BOVIS BCG 60 [hp_X]/59 mL; MUMPS VIRUS 60 [hp_X]/59 mL; CLOSTRIDIUM TETANI TOXOID ANTIGEN (FORMALDEHYDE INACTIVATED) 60 [hp_X]/59 mL; HUMAN VARICELLA-ZOSTER IMMUNE GLOBULIN 60 [hp_X]/59 mL
INACTIVE INGREDIENTS: ALCOHOL; WATER

X32

ACTIVE INGREDIENTS

Calcarea carbonica 3X, 6X, 9X, 12X, 30X, 60X
Echinacea angustifolia 3X, 6X, 9X, 12X, 30X
Silicea 3X, 6X, 9X, 12X, 30X, 60X
Thuja occidentalis 3X, 6X, 9X, 12X, 30X, 60X
Arsenicum album 6X, 9X, 12X, 30X, 60X
Sulphur 6X, 9X, 12X, 30X
Malandrinum 30X
and all the following at 60X, 100X, 200X:
DTP vaccine
Hepatitis A,B,C
Hib vaccine
MMR vaccine
OPV vaccine
Td vaccine
Varicella

QUESTIONS

Professional Formulas

PO Box 2034 Lake Oswego, OR 97035

INDICATIONS

For the temporary relief of fussiness, tiredness, loss of appetite, minor aches or pains, occasional headache, nausea, or vomiting due to sensitivity to vaccination.*

PURPOSE

*Claims based on traditional homeopathic practice, not accepted medical evidence. Not FDA evaluated.

WARNINGS

Persistent symptoms may be a sign of a serious condition. If symptoms persist or are accompanied by a fever, rash, or persistent headache, consult a doctor. Keep out of the reach of children. In case of overdose, get medical help or contact a poison control center right away. If pregnant or breastfeeding, ask a healthcare professional before use.

Keep out of the reach of children.

PREGNANCY OR BREAST FEEDING

If pregnant or breastfeeding, ask a healthcare professional before use.

DIRECTIONS

Place drops under tongue 30 minutes before/after meals. Adults and children 12 years and over: Take 10 drops up to 3 times per day. Consult a physician for use in children under 12 years of age.

OTHER INFORMATION

Tamper resistant. If seal is broken, do not use. After opening, close container tightly and store at room temperature away from heat.

INACTIVE INGREDIENTS

10% ethanol, 8% vegetable glycerin (from soy), purified water.

LABEL

Est 1985

Professional Formulas

Complementary Health

Childhood Immunization Detox

Homeopathic Remedy

2 FL. OZ. (59 mL)